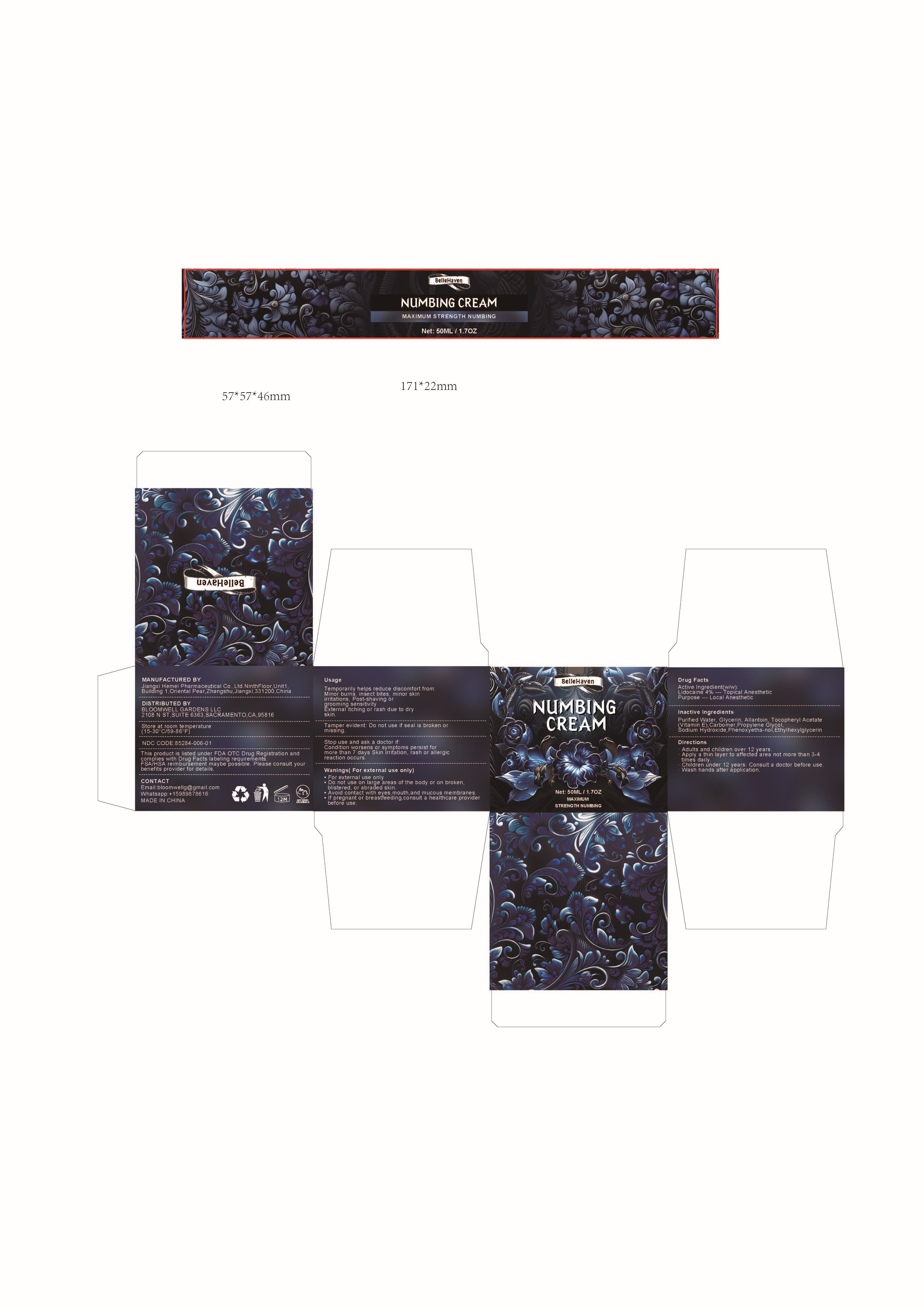 DRUG LABEL: numbing cream MAXIMUM STRENGTH
NDC: 85284-006 | Form: CREAM
Manufacturer: BLOOMWELL GARDENS LLC
Category: otc | Type: HUMAN OTC DRUG LABEL
Date: 20250725

ACTIVE INGREDIENTS: LIDOCAINE 4 g/100 g
INACTIVE INGREDIENTS: VITAMIN E POLYETHYLENE GLYCOL SUCCINATE; PROPYLENE GLYCOL; ALLANTOIN; PHENOXYETHANOL; GLYCERIN; WATER; CARBOMER; ETHYLHEXYLGLYCERIN; SODIUM HYDROXIDE

ACTIVE INGREDIENT

Lidocaine 4% --- Topical Anesthetic

INACTIVE INGREDIENT

Purified Water, Glycerin, Allantoin, Tocopheryl Acetate

(Vitamin E), Carbomer,Propylene Glycol,

Sodium Hydroxide, Phenoxyetha-nol, Ethylhexylglycerin

PURPOSE

Local anesthetic

INDICATIONS AND USAGE

Temporarily helps reduce discomfort from:
Minor burns, insect bites, minor skin
irritations, Post-shaving or grooming sensitivity
External itching or rash due to dry skin

WARNINGS

For external use only
• For external use only
• Do not use on large areas of the body or on broken,
blistered, or abraded skin.
• Avoid contact with eyes,mouth,and mucous membranes.
• If pregnant or breastfeeding,consult a healthcare provider
before use

Stop use and ask a doctor if:

Condition worsens or symptoms persist for more than 7 days Skin irritation, rash or allergic reaction occurs.

Keep out of reach of children. If swallowed, get medical help or contact a Poison Control Center right away

OTHER SAFETY INFORMATION

Tamper evident: Do not use if seal is broken or missing.

DOSAGE AND ADMINISTRATION

▪ Adults and children over 12 years:

▪ Apply a thin layer to affected area not more than 3–4 times daily

▪ Children under 12 years: Consult a doctor before use

▪ Wash hands after application